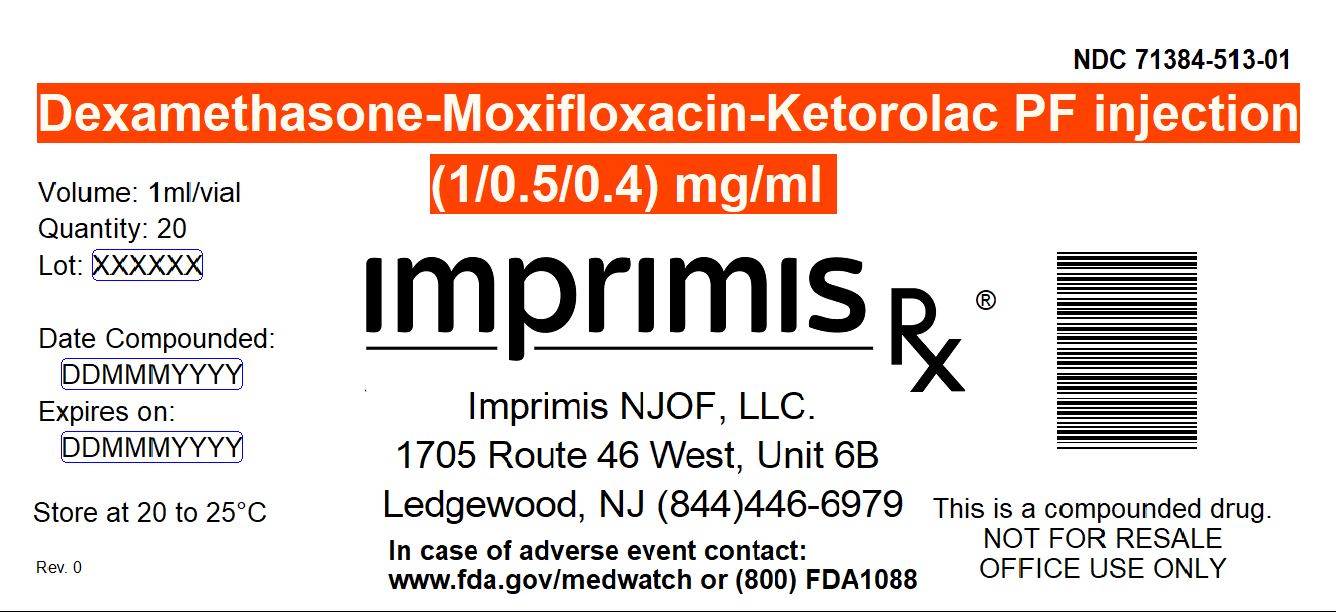 DRUG LABEL: Dex-Moxi-Ketor
NDC: 71384-513 | Form: INJECTION, SOLUTION
Manufacturer: Imprimis NJOF, LLC
Category: prescription | Type: HUMAN PRESCRIPTION DRUG LABEL
Date: 20200210

ACTIVE INGREDIENTS: DEXAMETHASONE SODIUM PHOSPHATE 1 mg/1 mL; MOXIFLOXACIN HYDROCHLORIDE MONOHYDRATE 0.5 mg/1 mL; KETOROLAC TROMETHAMINE 0.4 mg/1 mL

STORAGE AND HANDLING

Store at 20° to 25° C (68° to 77° F)